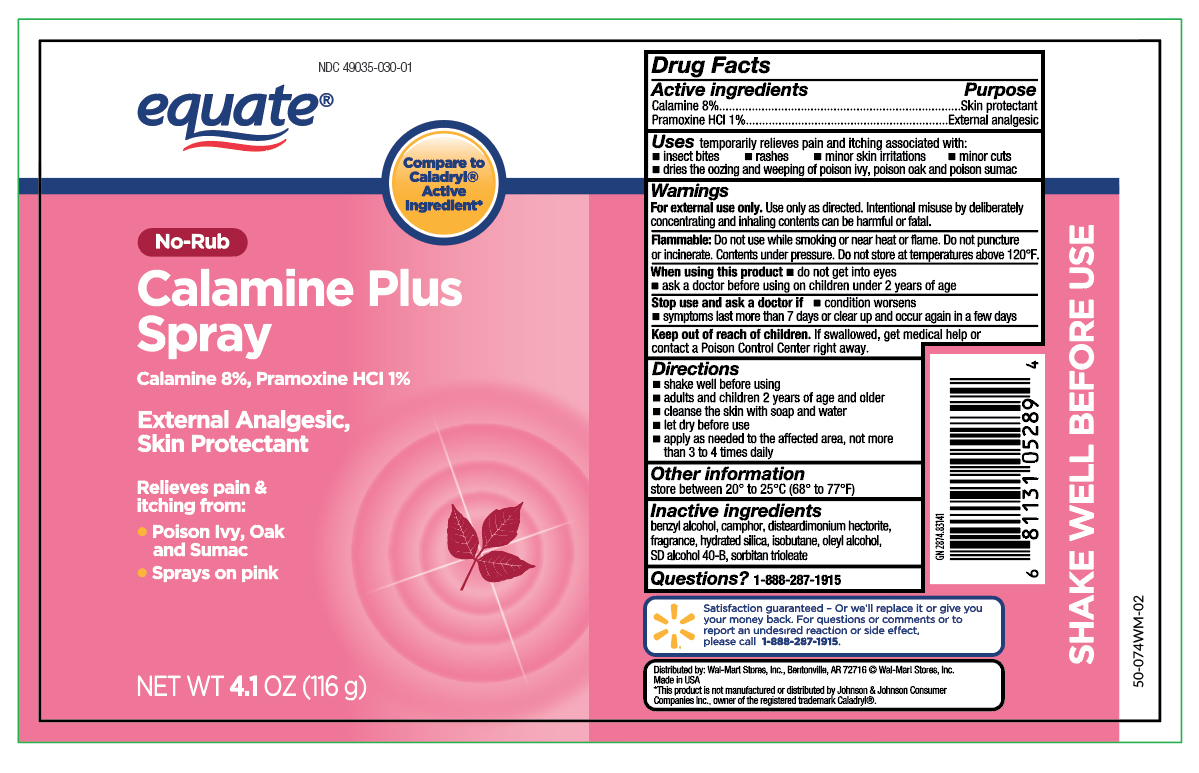 DRUG LABEL: Calamine Plus
NDC: 49035-030 | Form: AEROSOL, SPRAY
Manufacturer: Wal-Mart Stores, Inc.
Category: otc | Type: HUMAN OTC DRUG LABEL
Date: 20250621

ACTIVE INGREDIENTS: FERRIC OXIDE RED 0.345 mg/1 mL; PRAMOXINE HYDROCHLORIDE 2.72 mg/1 mL; ZINC OXIDE 24.16 mg/1 mL
INACTIVE INGREDIENTS: BENZYL ALCOHOL; CAMPHOR (SYNTHETIC); HYDRATED SILICA; ISOBUTANE; OLEYL ALCOHOL; SORBITAN TRIOLEATE

Equate Calamine Plus Spray

Active Ingredients

Calamine 8%

Pramoxine HCL 1%

Purpose

Skin protectant

External analgesic

Keep out of reach of children. If swallowed, get medical help or contact a Poison Control Center right away.

Uses

Uses temporarily relieves pain and itching associated with:

- insect bites
- rashes
- minor skin irritations
- minor cuts
- dries the oozing and weeping of poison ivy, poison oak and poison sumac

Warnings

For external use only. Use only as directed. Intentional misuse by deliberately concentrating and inhaling contents can be harmful or fatal.

Flammable

Flammable: Do not use while smoking, or near heat or flame. Do not puncture or incinerate.Contents under pressure. Do not store at temperatures above 120 degrees F.

When using this product

- do not get into eyes
- ask a doctor before using on children under 2 years of age

Stop use and ask a doctor if

- condition worsens
- symptoms last more than 7 days or clear up and occur again in a few days

Directions

- shake well before using
- adults and children 2 years of age and older
- cleanse the skin with soap and water
- let dry before use
- apply as needed to the affected area, not more than 3 to 4 times a day

Other information

store between 20 degrees to 25 degrees C (68 degrees to 77 degrees F)

Inactive ingredients

benzyl alcohol, camphor, disteardimonium hectorite, fragrance, hydrated silica, isobutane, oleyl alcohol, SD alcohol 40-B, sorbitan trioleate

Questions?

Questions ? Call 1-866-964-0939

Principal Display Panel

Equate

No-Rub

Calamine Plus Spray

Calamine 8%, Pramoxine HCL 1%

External Analgesic,

Skin Protectant

Relieves pain & itching from:

- Poison Ivy, Oak and Sumac
- Sprays on pink

NET WT 4.1 OZ (116 g)